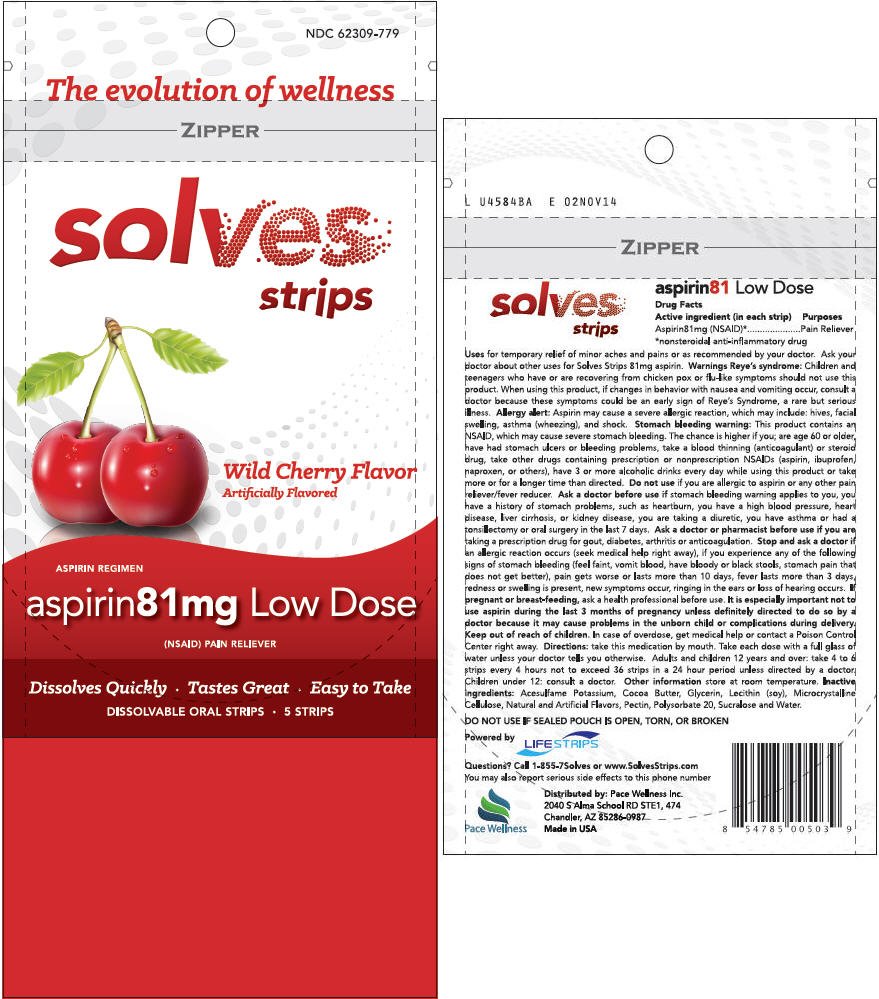 DRUG LABEL: Solves - aspirin 
NDC: 62309-779 | Form: STRIP
Manufacturer: Pace Wellness Inc.
Category: otc | Type: HUMAN OTC DRUG LABEL
Date: 20150129

ACTIVE INGREDIENTS: Aspirin 81 mg/1 1
INACTIVE INGREDIENTS: Pectin; Water; Glycerin; Sucralose; Polysorbate 20; Lecithin, Soybean; Cellulose, Microcrystalline; Cocoa Butter; Acesulfame Potassium

Solves Strips - aspirin 81 mg
Cherry

Drug Facts

Active ingredient (in each strip)

Aspirin 81mg (NSAID) [nonsteroidal anti-inflammatory drug]

Purposes

Pain Reliever

Uses

for temporary relief of minor aches and pains or as recommended by your doctor. Ask your doctor about other uses for Solves Strips 81mg aspirin.

Warnings

Reye's syndrome

Children and teenagers who have or are recovering from chicken pox or flu-like symptoms should not use this product.

When using this product, if changes in behavior with nausea and vomiting occur, consult a doctor because these symptoms could be an early sign of Reye's Syndrome, a rare but serious illness.

Allergy alert

Aspirin may cause a severe allergic reaction, which may include: hives, facial swelling, asthma (wheezing), and shock.

Stomach bleeding warning

This product contains an NSAID, which may cause severe stomach bleeding. The chance is higher if you; are age 60 or older, have had stomach ulcers or bleeding problems, take a blood thinning (anticoagulant) or steroid drug, take other drugs containing prescription or nonprescription NSAIDs (aspirin, ibuprofen, naproxen, or others), have 3 or more alcoholic drinks every day while using this product or take more or for a longer time than directed.

Do not use if you are allergic to aspirin or any other pain reliever/fever reducer.

Ask a doctor before use if stomach bleeding warning applies to you, you have a history of stomach problems, such as heartburn, you have a high blood pressure, heart disease, liver cirrhosis, or kidney disease, you are taking a diuretic, you have asthma or had a tonsillectomy or oral surgery in the last 7 days.

Ask a doctor or pharmacist before use if you are taking a prescription drug for gout, diabetes, arthritis or anticoagulation.

STOP USE

Stop and ask a doctor if an allergic reaction occurs (seek medical help right away), if you experience any of the following signs of stomach bleeding (feel faint, vomit blood, have bloody or black stools, stomach pain that does not get better), pain gets worse or lasts more than 10 days, fever lasts more than 3 days, redness or swelling is present, new symptoms occur, ringing in the ears or loss of hearing occurs.

PREGNANCY OR BREAST FEEDING

If pregnant or breast-feeding, ask a health professional before use. It is especially important not to use aspirin during the last 3 months of pregnancy unless definitely directed to do so by a doctor because it may cause problems in the unborn child or complications during delivery.

Keep out of reach of children. In case of overdose, get medical help or contact a Poison Control Center right away.

Directions

take this medication by mouth. Take each dose with a full glass of water unless your doctor tells you otherwise. Adults and children 12 years and over: take 4 to 6 strips every 4 hours not to exceed 36 strips in a 24 hour period unless directed by a doctor. Children under 12: consult a doctor.

Other information

store at room temperature.

Inactive ingredients

Acesulfame Potassium, Cocoa Butter, Glycerin, Lecithin (soy), Microcrystalline Cellulose, Natural and Artificial Flavors, Pectin, Polysorbate 20, Sucralose, Water.

DO NOT USE IF SEALED POUCH IS OPEN, TORN, OR BROKEN

Questions?

Call 1-855-7Solves or www.SolvesStrips.com
You may also report serious side effects to this phone number

Distributed by: Pace Wellness Inc.
2040 S Alma School RD STE1, 474
Chandler, AZ 85286-0987

PRINCIPAL DISPLAY PANEL - 5 Strip Pouch

NDC 62309-779

The evolution of wellness

ZIPPER

solves
strips

Wild Cherry Flavor
Artificially Flavored

ASPIRIN REGIMEN

aspirin81mg Low Dose

(NSAID) PAIN RELIEVER

Dissolves Quickly • Tastes Great • Easy to Take

DISSOLVABLE ORAL STRIPS • 5 STRIPS